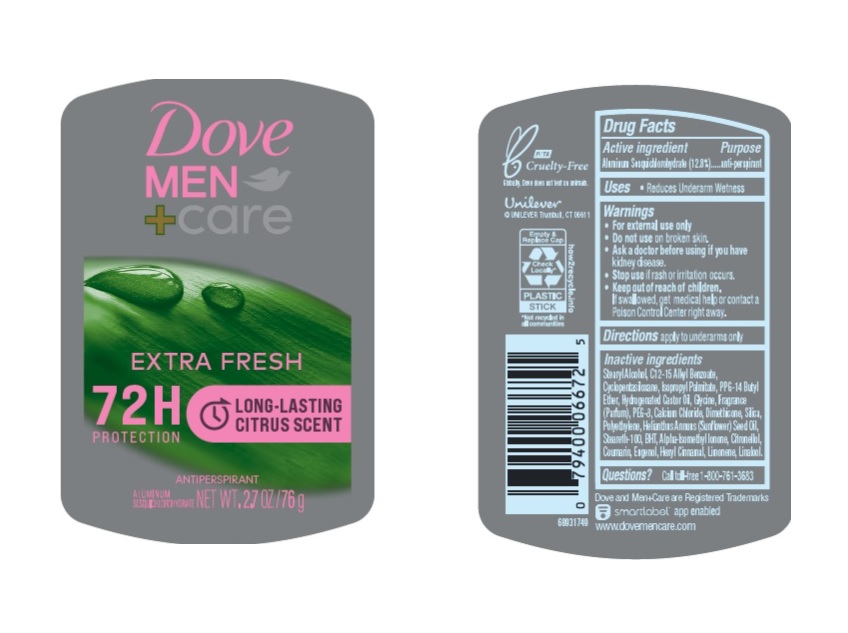 DRUG LABEL: Dove
NDC: 64942-2053 | Form: STICK
Manufacturer: Conopco Inc. d/b/a/ Unilever
Category: otc | Type: HUMAN OTC DRUG LABEL
Date: 20241106

ACTIVE INGREDIENTS: ALUMINUM SESQUICHLOROHYDRATE 12.8 g/100 g
INACTIVE INGREDIENTS: CYCLOMETHICONE 5; HYDROGENATED CASTOR OIL; BUTYLATED HYDROXYTOLUENE; PPG-14 BUTYL ETHER; STEARYL ALCOHOL; SUNFLOWER OIL; SILICON DIOXIDE; ALKYL (C12-15) BENZOATE; DIMETHICONE; STEARETH-100; POLYETHYLENE GLYCOL 400; ISOPROPYL PALMITATE; .BETA.-CITRONELLOL, (R)-; GLYCINE; EUGENOL; COUMARIN; ISOMETHYL-.ALPHA.-IONONE; LINALOOL, (+/-)-; .ALPHA.-HEXYLCINNAMALDEHYDE; LIMONENE, (+)-; HIGH DENSITY POLYETHYLENE

Dove Men + Care Extra Fresh 72H Antiperspirant

DOVE MEN + CARE EXTRA FRESH 72H ANTIPERSPIRANT - aluminum sesquichlorohydrate stick

Dove Men plus Care Extra Fresh 48HR+Comfort Antiperspirant

Drug Facts

Active ingredient

Aluminum Sesquichlorohydrate (12.8)

Purpose

antiperspirant

Uses

reduces underarm wetness

Warnings

• For external use only.
• Do not use on broken skin .
• Ask a doctor before use if you have kidney disease.
• Stop use if rash or irritation occurs.

• Keep out of reach of children.

If swallowed, get medical help or contact a Poison Control Center right away.

Directions

apply to underarms only

Inactive ingredients

Stearyl Alcohol, C12-15 Alkyl Benzoate, Cyclopentasiloxane, Isopropyl Palmitate, PPG-14 Butyl Ether, Hydrogenated Castor Oil, Glycine, Fragrance (Parfum), PEG-8, Calcium Chloride, Dimethicone, Silica, Polyethylene, Helianthus Annuus (Sunflower) Seed Oil, Steareth-100, BHT, Alpha-Isomethyl Ionone, Citronellol, Coumarin, Eugenol, Hexyl Cinnamal, Limonene, Linalool .

Questions?

Call toll-free 1-800-761-3683